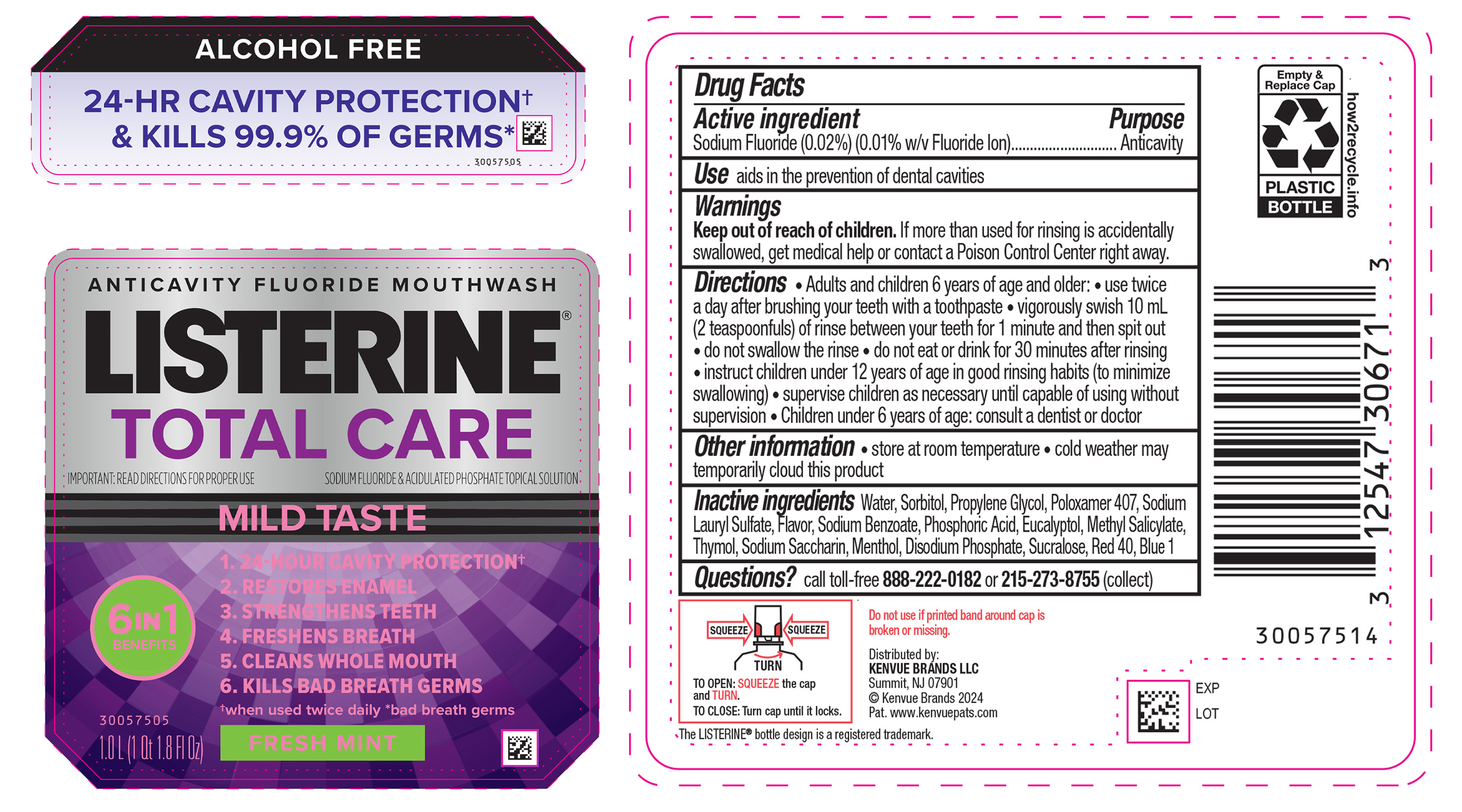 DRUG LABEL: Listerine Total Care Alcohol Free Anticavity Fluoride Mouthwash Fresh Mint
NDC: 69968-0924 | Form: MOUTHWASH
Manufacturer: Kenvue Brands LLC
Category: otc | Type: HUMAN OTC DRUG LABEL
Date: 20250505

ACTIVE INGREDIENTS: SODIUM FLUORIDE 0.1 mg/1 mL
INACTIVE INGREDIENTS: WATER; SORBITOL; PROPYLENE GLYCOL; POLOXAMER 407; EUCALYPTOL; METHYL SALICYLATE; THYMOL; PHOSPHORIC ACID; MENTHOL, UNSPECIFIED FORM; SODIUM PHOSPHATE, DIBASIC, ANHYDROUS; SACCHARIN SODIUM; SUCRALOSE; FD&C RED NO. 40; FD&C BLUE NO. 1; SODIUM LAURYL SULFATE; SODIUM BENZOATE

Listerine Total Care Alcohol Free Anticavity Fluoride Mouthwash Fresh Mint

Drug Facts

Active ingredient

Sodium Fluoride (0.02%) (0.01% w/v Fluoride Ion)

Purpose

Anticavity

Use

aids in the prevention of dental cavities

Warnings

Keep out of reach of children. If more than used for rinsing is accidentally swallowed, get medical help or contact a Poison Control Center right away.

Directions

- Adults and children 6 years of age and older:
  - use twice a day after brushing your teeth with a toothpaste.
  - vigorously swish 10 mL (2 teaspoonfuls) of rinse between your teeth for 1 minute and then spit out
  - do not swallow the rinse.
  - do not eat or drink for 30 minutes after rinsing
  - instruct children under 12 years of age in good rinsing habits (to minimize swallowing)
  - supervise children as necessary until capable of using without supervision.
- Children under 6 years of age: consult a dentist or doctor

Other information

- store at room temperature
- cold weather may temporarily cloud this product

Inactive Ingredients

Water, Sorbitol, Propylene Glycol, Poloxamer 407, Sodium Lauryl Sulfate, Flavor, Sodium Benzoate, Phosphoric Acid, Eucalyptol, Methyl Salicylate, Thymol, Sodium Saccharin, Menthol, Disodium Phosphate, Sucralose, Red 40, Blue 1

Questions?

call toll-free 888-222-0182 or 215-273-8755 (collect)

Distributed by:
Kenvue Brands LLC

Summit, NJ 07901

PRINCIPAL DISPLAY PANEL - 1000 mL Bottle Label

ALCOHOL FREE

24-HR CAVITY PROTECTION†

& KILLS 99.9% OF GERMS*

ANTICAVITY FLUORIDE MOUTHWASH

LISTERINE®

TOTAL CARE

IMPORTANT: READ DIRECTIONS FOR PROPER USE

SODIUM FLUORIDE & ACIDULATED PHOSPHATE TOPICAL SOLUTION

MILD TASTE

6 IN 1

BENEFITS

1. 24-HOUR CAVITY PROTECTION†

2. RESTORES ENAMEL

3. STRENGTHENS TEETH

4. FRESHENS BREATH

5. CLEANS WHOLE MOUTH

6. KILLS BAD BREATH GERMS

†when used twice daily *bad breath germs

FRESH MINT

1.0 L (1 Qt 1.8 Fl Oz)